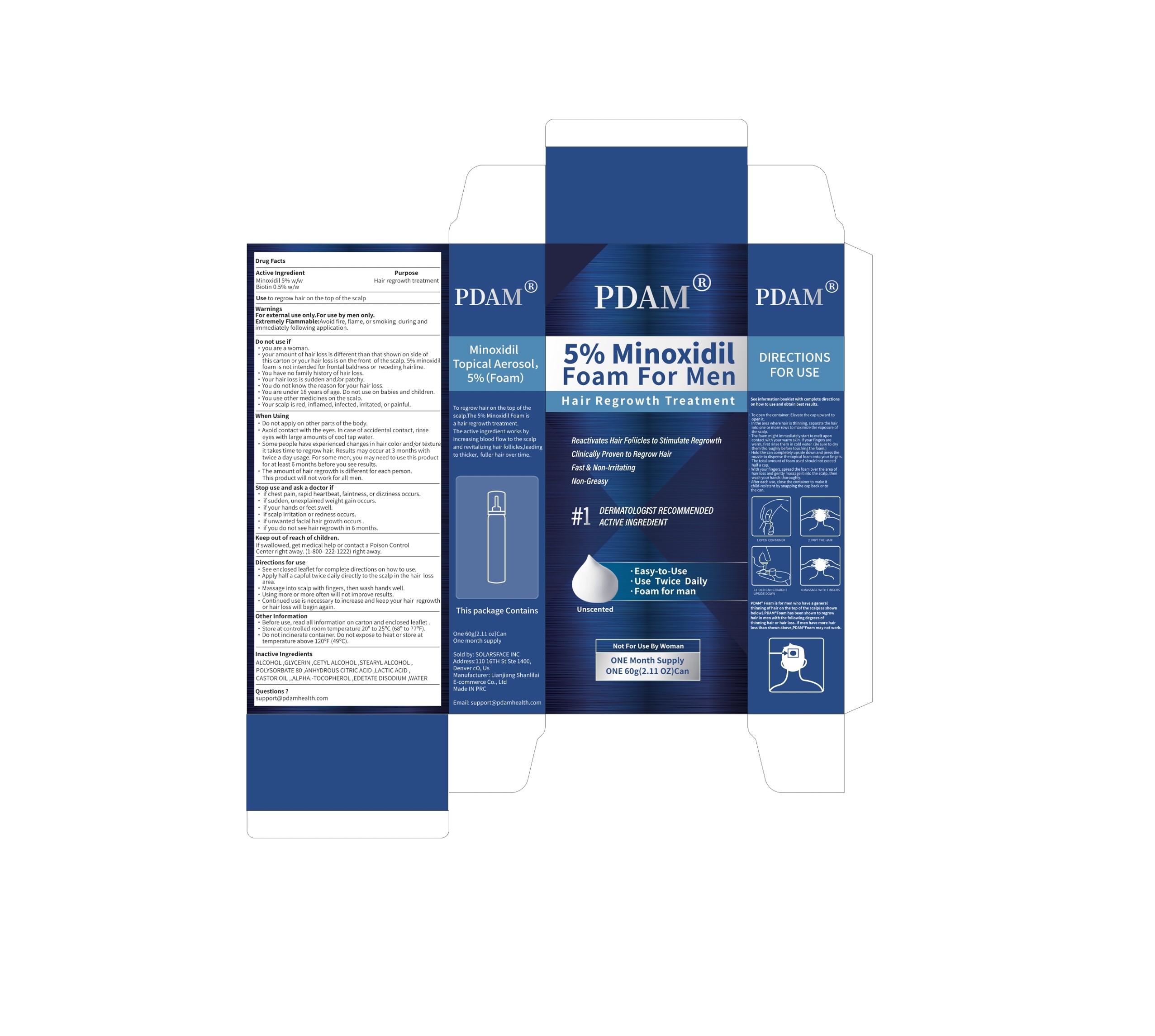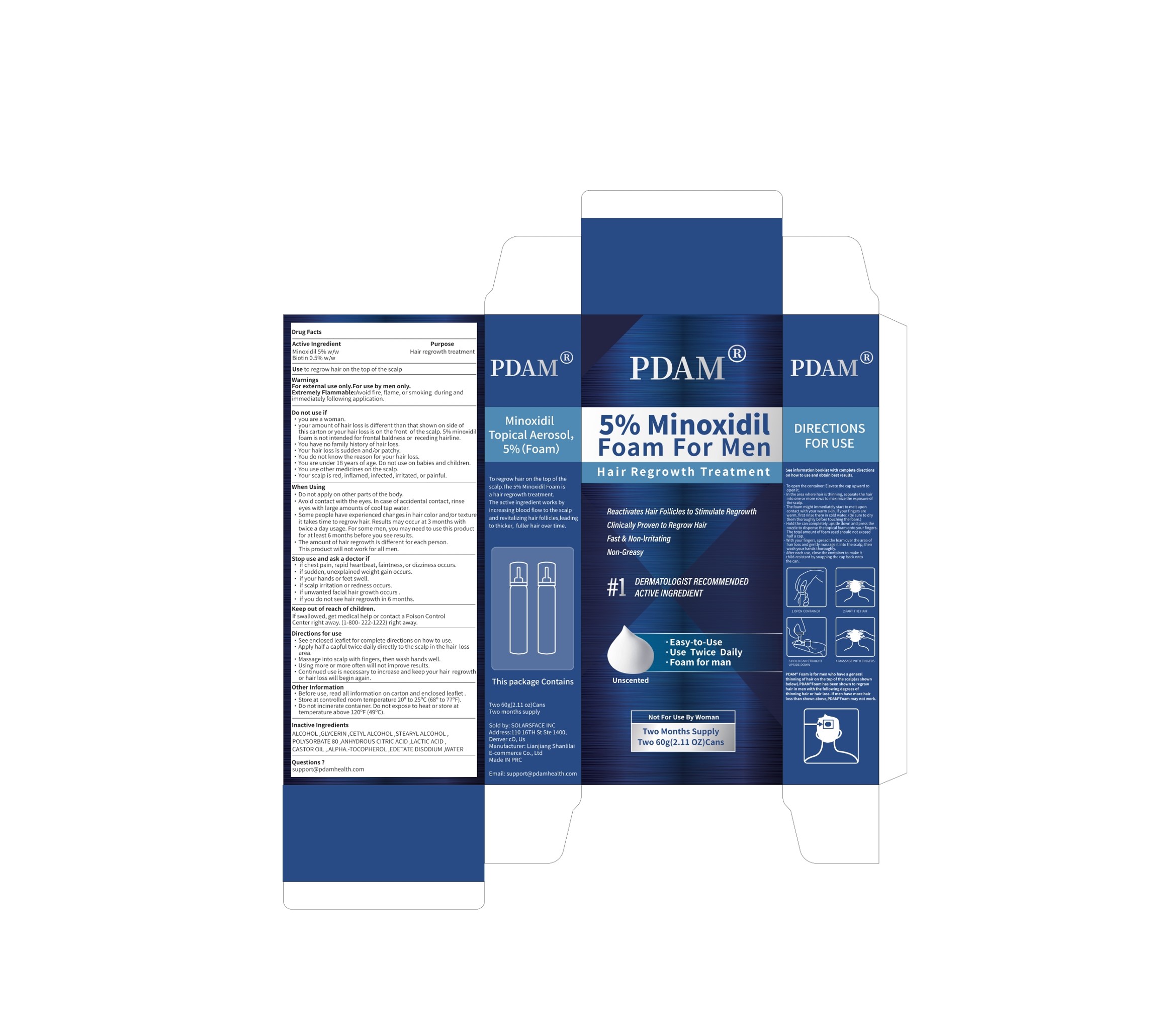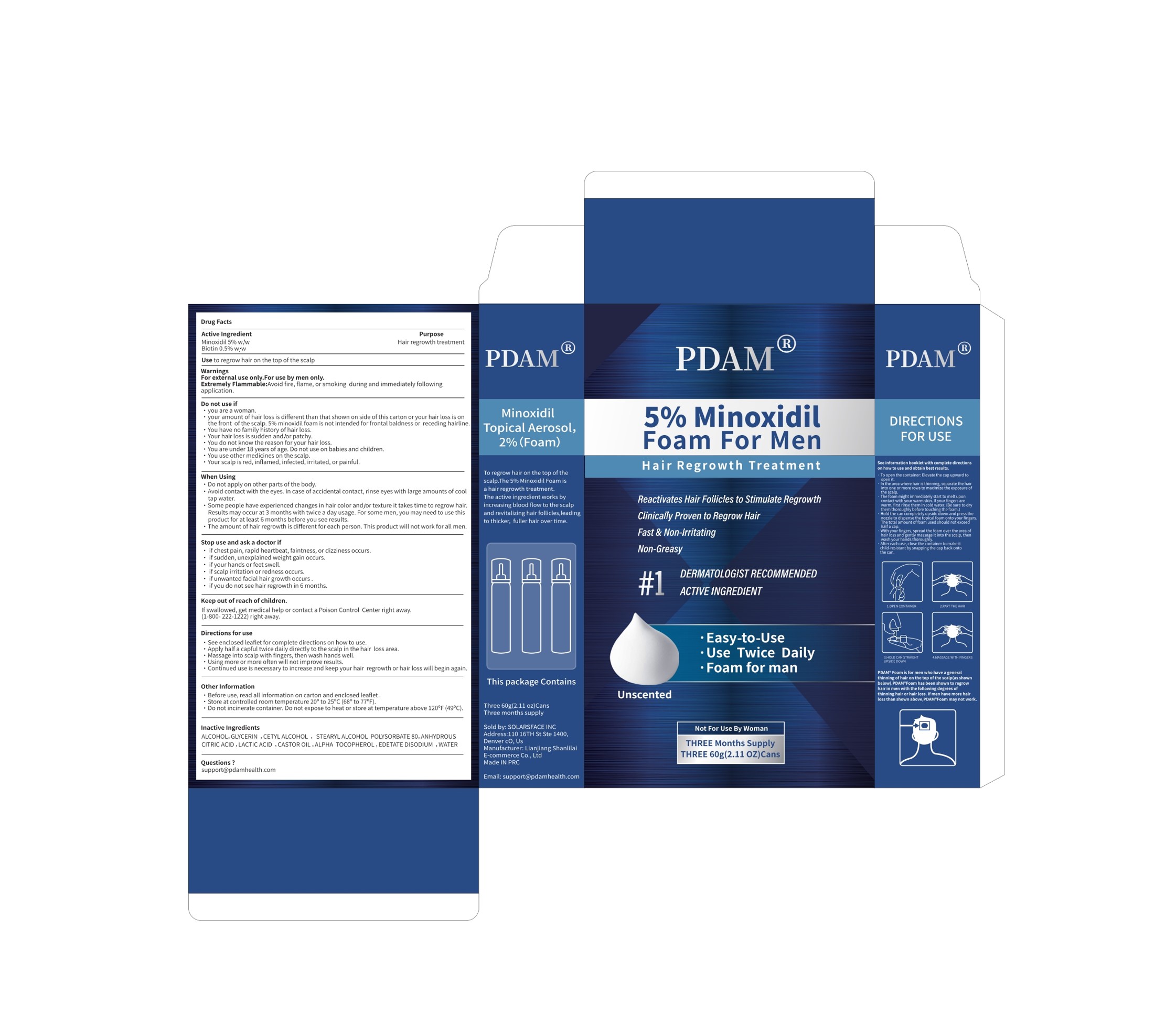 DRUG LABEL: 5% Minoxidil Hair Regrowth Foam
NDC: 85038-003 | Form: AEROSOL, FOAM
Manufacturer: Lianjiang Shanlilai E-commerce Co., Ltd.
Category: otc | Type: HUMAN OTC DRUG LABEL
Date: 20241211

ACTIVE INGREDIENTS: MINOXIDIL 5 g/100 g; BIOTIN 0.5 g/100 g
INACTIVE INGREDIENTS: LACTIC ACID; .ALPHA.-TOCOPHEROL; CETYL ALCOHOL; ALCOHOL; STEARYL ALCOHOL; GLYCERIN; POLYSORBATE 80; ANHYDROUS CITRIC ACID; CASTOR OIL; EDETATE DISODIUM; WATER

5% Minoxidil Hair Regrowth Foam

5% Minoxidil Hair Regrowth Foam

ACTIVE INGREDIENT

Minoxidil 5%
Biotin 0.5%

PURPOSE

Hair regrowth treatment

INDICATIONS AND USAGE

Use to regrow hair on the top of the scalp

WARNINGS

For external use only. For use by men only.
Extremely Flammable:Avoid fire, flame, or smoking during andimmediately following application.

DO NOT USE

you are a woman.
your amount of hair loss is different than that shown on side ofthis carton or your hair loss is on the front of the scalp.5% minoxidilfoam is not intended for frontal baldness or receding hairline.
You have no family history of hair loss.
Your hair loss is sudden andjor patchy.
You do not know the reason for your hair loss.
You are under 18 years of age. Do not use on babies and children.
You use other medicines on the scalp.
Your scalp is red, inflamed, infected, irritated, or painful.

WHEN USING

Do not apply on other parts of the body.
Avoid contact with the eyes. in case of accidental contact, rinseeyes with large amounts of cool tap water.
Some people have experienced changes in hair color and,;or textureit takes time to regrow hair, Results may occur at 3 months withtwice a day usage. For some men, you may need to use this productfor at least 6 months before you see results.
The amount of hair regrowth is different for each person.This product will not work for all men.

STOP USE

if chest pain, rapid heartbeat, faintness, or dizziness occurs.
if sudden, unexplained weight gain occurs.
if your hands or feet swell.
if scalp irritation or redness occurs.
if unwanted facial hair growth occurs.
if you do not see hair regrowth in 6 months.

KEEP OUT OF REACH OF CHILDREN

lf swallowed, get medical help or contact a Poison ControlCenter right away.(1-800-222-1222)right away.

DOSAGE AND ADMINISTRATION

See enclosed leaflet for complete directions on how to use.
Apply half a capful twice daily directly to the scalp in the hair lossarea.
Massage into scalp with fingers, then wash hands well.
Using more or more often will not improve results.
Continued use is necessary to increase and keep your hair regrowthor hair loss will begin again.

STORAGE AND HANDLING

Before use, read all information on carton and enclosed leaflet

Store at controlled room temperature 20° to 25°C (68° to 77°F).

Do not incinerate container. Do not expose to heat or store attemperature above 120°F(49°C).

INACTIVE INGREDIENT

ALCOHOL
GLYCERIN
CETYL ALCOHOL
STEARYL ALCOHOL
POLYSORBATE 80
ANHYDROUS CITRIC ACID
LACTIC ACID
CASTOR OIL
.ALPHA.-TOCOPHEROL
EDETATE DISODIUM
WATER